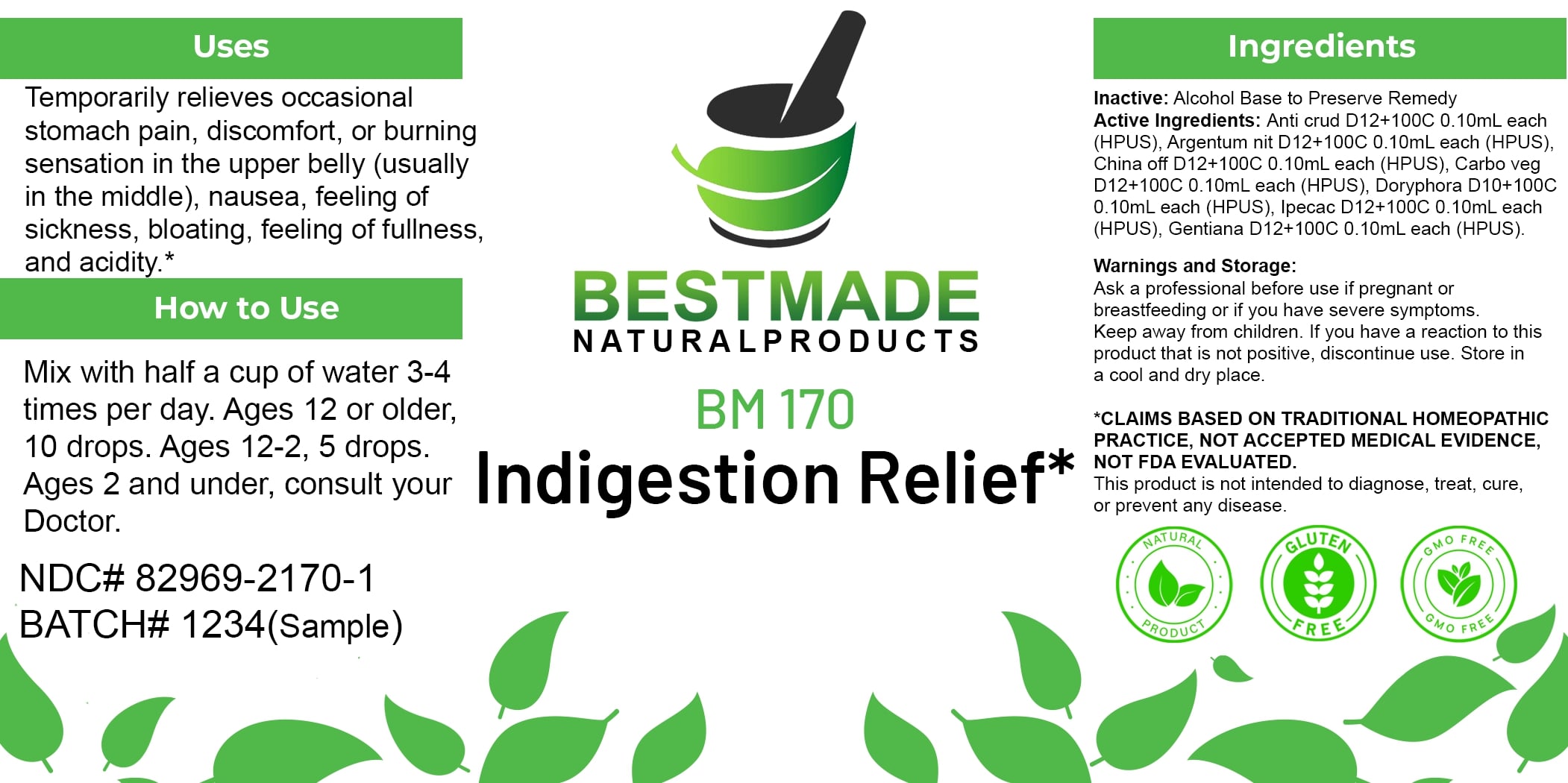 DRUG LABEL: Bestmade Natural Products BM170
NDC: 82969-2170 | Form: LIQUID
Manufacturer: Bestmade Natural Products
Category: homeopathic | Type: HUMAN OTC DRUG LABEL
Date: 20250219

ACTIVE INGREDIENTS: ANTIMONY TRISULFIDE 30 [hp_C]/30 [hp_C]; LEPTINOTARSA DECEMLINEATA 30 [hp_C]/30 [hp_C]; SILVER NITRATE 30 [hp_C]/30 [hp_C]; ACTIVATED CHARCOAL 30 [hp_C]/30 [hp_C]; GENTIANA LUTEA ROOT 30 [hp_C]/30 [hp_C]; CINCHONA OFFICINALIS BARK 30 [hp_C]/30 [hp_C]; IPECAC 30 [hp_C]/30 [hp_C]
INACTIVE INGREDIENTS: ALCOHOL 30 [hp_C]/30 [hp_C]

BM170

DOSAGE AND ADMINISTRATION

How to Use

Mix with half a cup of water 3-4 times per day. Ages 12 or older, 10 drops. Ages 12-2, 5 drops. Ages 2 and under, consult your Doctor.

INACTIVE INGREDIENT

Ingredients

Inactive: Alcohol Base to Preserve Remedy

ACTIVE INGREDIENT

Active Ingredients: Ant crud D12+100C 0.10ml each (HPUS), Argentum nit D12+100C 0.10ml each (HPUS), China off D12+100C 0.10ml each (HPUS), Carbo veg D12+100C 0.10ml each (HPUS), Doryphora D10+100C 0.10ml each (HPUS), Ipecac D12+100C 0.10ml each (HPUS), Gentiana D12+100C 0.10ml each (HPUS)

Uses

Temporarily relieves occasional stomach pain, discomfort, or burning sensation in the upper belly (usually in the middle), nausea, feeling of sickness, bloating, feeling of fullness, and acidity.*

*CLAIMS BASED ON TRADITIONAL HOMEOPATHIC PRACTICE. NOT ACCEPTED MEDICAL EVIDENCE. NOT FDA EVALUATED.

This product is not intended to diagnose, treat, cure, or prevent any disease.

Uses

Temporarily relieves occasional stomach pain, discomfort, or burning sensation in the upper belly (usually in the middle), nausea, feeling of sickness, bloating, feeling of fullness, and acidity.*

*CLAIMS BASED ON TRADITIONAL HOMEOPATHIC PRACTICE. NOT ACCEPTED MEDICAL EVIDENCE. NOT FDA EVALUATED.

This product is not intended to diagnose, treat, cure, or prevent any disease.

KEEP OUT OF REACH OF CHILDREN

Warnings and Storage:

Ask a professional before use if pregnant or breastfeeding or if you have severe symptoms. Keep away from children. If you have a reaction to this product that is not positive, discontinue use. Store in a cool and dry place.

Warnings and Storage:

Ask a professional before use if pregnant or breastfeeding or if you have severe symptoms. Keep away from children. If you have a reaction to this product that is not positive, discontinue use. Store in a cool and dry place.

*CLAIMS BASED ON TRADITIONAL HOMEOPATHIC PRACTICE. NOT ACCEPTED MEDICAL EVIDENCE. NOT FDA EVALUATED.

This product is not intended to diagnose, treat, cure, or prevent any disease.

Entire package label